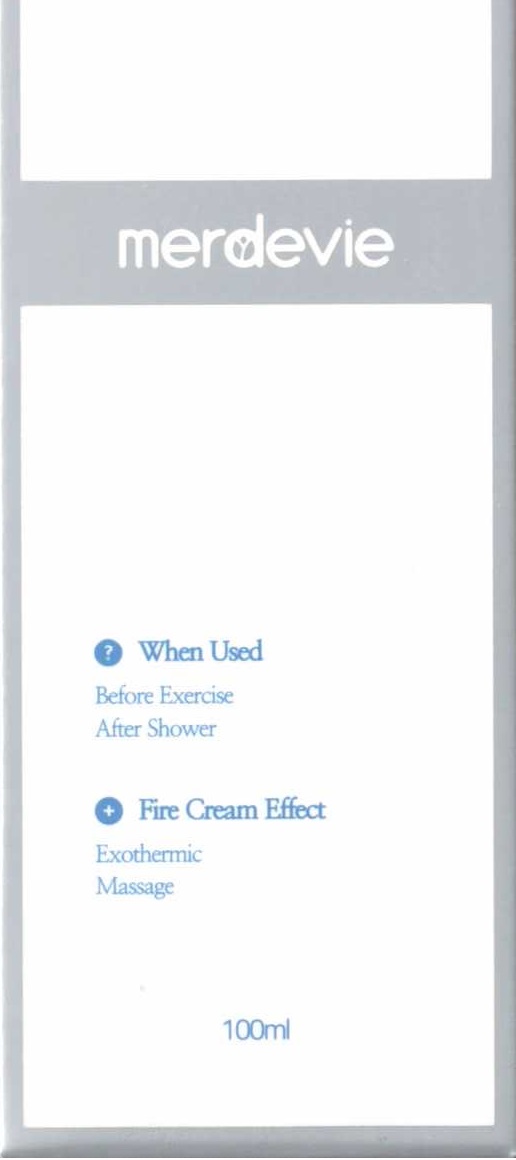 DRUG LABEL: MERDEVIE FIRECREAM
NDC: 80766-0002 | Form: CREAM
Manufacturer: Lady House Co., Ltd.
Category: otc | Type: HUMAN OTC DRUG LABEL
Date: 20201016

ACTIVE INGREDIENTS: GLYCERIN 5 g/100 mL
INACTIVE INGREDIENTS: WATER

Drug Facts

ACTIVE INGREDIENT

glycerin

PURPOSE

skin protectant

KEEP OUT OF REACH OF THE CHILDREN

INDICATIONS AND USAGE

apply proper amount to the skin

WARNINGS

■ For external use only.

■ Do not use in eyes.

■ lf swallowed, get medical help promptly.

■ Stop use, ask doctor lf irritation occurs.

■ Keep out of reach of children.

DOSAGE AND ADMINISTRATION

for external use only

INACTIVE INGREDIENT

water, butylene glyucol, etc.